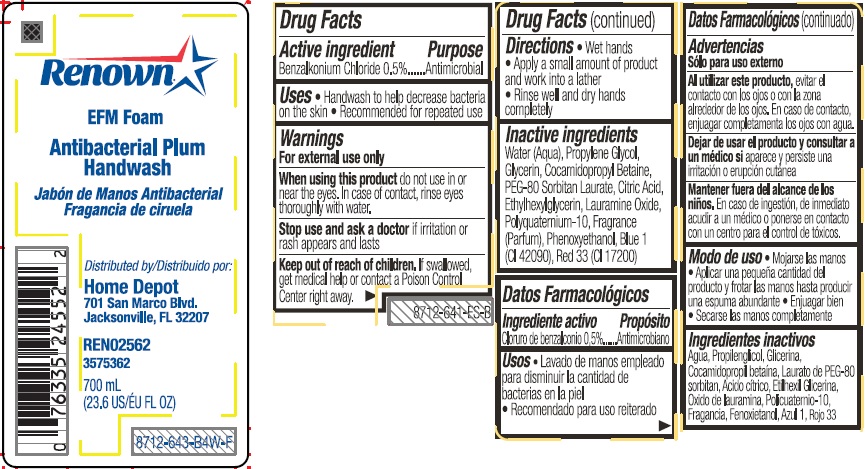 DRUG LABEL: RENOWN Antibacterial Plum Handwash
NDC: 42584-0400 | Form: LIQUID
Manufacturer: Home Depot U.S.A., Inc.
Category: otc | Type: HUMAN OTC DRUG LABEL
Date: 20260113

ACTIVE INGREDIENTS: BENZALKONIUM CHLORIDE 0.005 mg/1 mL
INACTIVE INGREDIENTS: WATER; PROPYLENE GLYCOL; GLYCERIN; COCAMIDOPROPYL BETAINE; PEG-80 SORBITAN LAURATE; CITRIC ACID MONOHYDRATE; ETHYLHEXYLGLYCERIN; LAURAMINE OXIDE; POLYQUATERNIUM-10 (10000 MPA.S AT 2%); PHENOXYETHANOL; FD&C BLUE NO. 1; D&C RED NO. 33

RENOWN® Antibacterial Plum Handwash

Active ingredient

Benzalkonium Chloride 0.5%

Purpose

Antimicrobial

Uses

• Handwash to help decrease bacteria on the skin

• Recommended for repeated use

Warnings

For external use only

WHEN USING

When using this productdo not use in or near the eyes. In case of contact, rinse eyes thoroughly with water.

Stop use and ask a doctor ifirritation or rash appears and lasts

Keep out of reach of children.If swallowed, get medical help or contact a Poison Control Center right away.

Directions

• Wet hands

• Apply a small amount of product and work into a lather

• Rinse well and dry hands completely

Inactive Ingredients

Water (Aqua), Propylene Glycol, Glycerin, Cocamidopropyl Betaine, PEG-80 Sorbitan Laurate, Citric Acid, Ethylhexylglycerin, Lauramine Oxide, Polyquaternium-10, Fragrance (Parfum), Phenoxyethanol, Blue 1 (CI 42090), Red 33 (CI 17200)